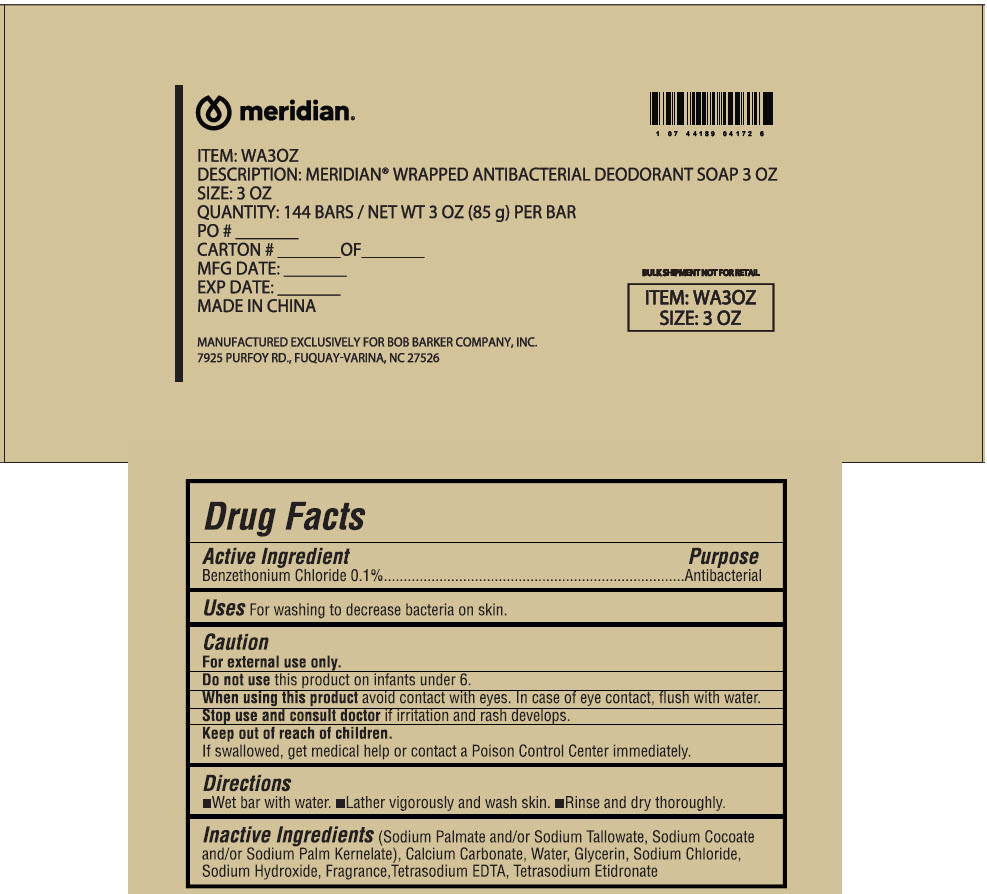 DRUG LABEL: Meridian wrapped antibacterial deodorant
NDC: 53247-141 | Form: SOAP
Manufacturer: Bob Barker Company Inc.
Category: otc | Type: HUMAN OTC DRUG LABEL
Date: 20250721

ACTIVE INGREDIENTS: BENZETHONIUM CHLORIDE 0.1 g/100 g
INACTIVE INGREDIENTS: Sodium Palmate; SODIUM TALLOWATE, BEEF; Sodium Cocoate; Sodium Palm Kernelate; Calcium Carbonate; Water; Glycerin; Sodium Chloride; Sodium Hydroxide; EDETATE SODIUM; ETIDRONATE TETRASODIUM

Meridian® wrapped antibacterial deodorant soap

Drug Facts

Active Ingredient

Benzethonium Chloride 0.1%

Purpose

Antibacterial

Uses

For washing to decrease bacteria on skin.

Caution

For external use only.

Do not use this product on infants under 6.

When using this product avoid contact with eyes. In case of eye contact, flush with water.

Stop use and consult doctor if irritation and rash develops.

Keep out of reach of children.

If swallowed, get medical help or contact a Poison Control Center immediately.

Directions

- Wet bar with water.
- Lather vigorously and wash skin.
- Rinse and dry thoroughly.

Inactive Ingredients

(Sodium Palmate and/or Sodium Tallowate, Sodium Cocoate and/or Sodium Palm Kernelate), Calcium Carbonate, Water, Glycerin, Sodium Chloride, Sodium Hydroxide, Fragrance, Tetrasodium EDTA, Tetrasodium Etidronate

PRINCIPAL DISPLAY PANEL - 144 Bar Cello Pack Case Label

meridian®

ITEM: WA3OZ

DESCRIPTION: MERIDIAN® WRAPPED ANTIBACTERIAL DEODORANT SOAP 3 OZ

SIZE: 3 OZ

QUANTITY: 144 BARS / NET WT 3 OZ (85 g) PER BAR

PO # __________

CARTON # ________OF________

MFG DATE: ___________

EXP DATE: __________

MADE IN CHINA

BULK SHIPMENT NOT FOR RETAIL

ITEM: WA3OZ
SIZE: 3 OZ

MANUFACTURED EXCLUSIVELY FOR BOB BARKER COMPANY, INC.
7925 PURFOY RD., FUQUAY-VARINA, NC 27526